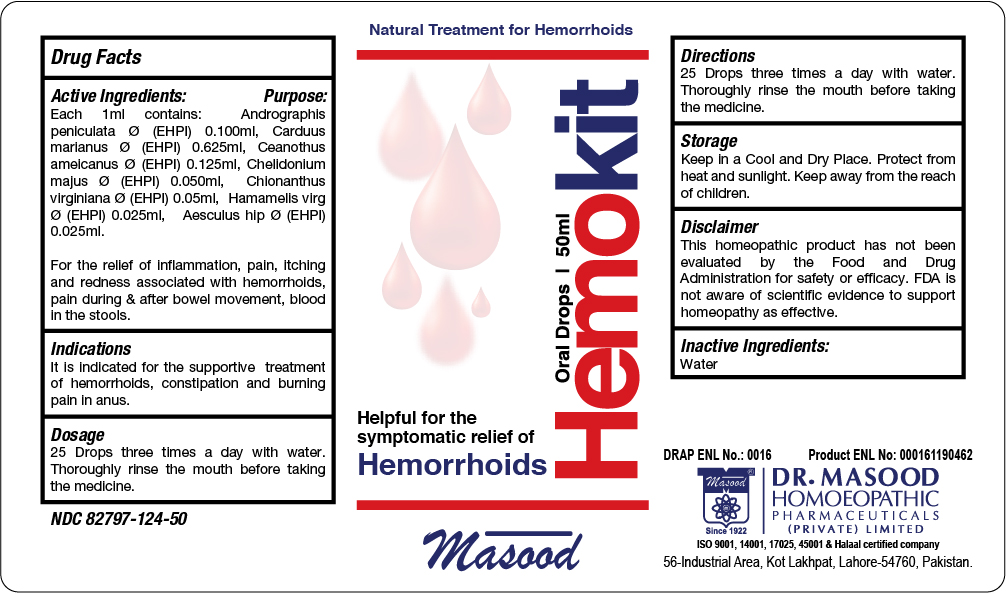 DRUG LABEL: Hemokit Oral Drops for Hemorrhoids
NDC: 82797-124 | Form: LIQUID
Manufacturer: Dr. Masood Homeopathic Pharmaceuticals Private Limited
Category: homeopathic | Type: HUMAN OTC DRUG LABEL
Date: 20240319

ACTIVE INGREDIENTS: CHELIDONIUM MAJUS WHOLE 0.05 mg/1 mL; HAMAMELIS VIRGINIANA ROOT BARK/STEM BARK 0.025 mg/1 mL; ANDROGRAPHIS PANICULATA WHOLE 0.1 mg/1 mL; MILK THISTLE 0.625 mg/1 mL; AESCULUS HIPPOCASTANUM BARK 0.025 mg/1 mL; CEANOTHUS AMERICANUS WHOLE 0.125 mg/1 mL; CHIONANTHUS VIRGINICUS WHOLE 0.05 mg/1 mL
INACTIVE INGREDIENTS: WATER 1 mL/1 mL

Keep Out of Reach of Children

Indications and Usage

It is indicated for the supportive treatment of hemorrhoids, constipation an dburning pain in anus

Dosage and Administration

25 Drops three times a day with water. Thoroughly rinse the mouth before taking

the medicine.

Storage

Keep in a Cool and Dry Place. Protect from heat and sunlight

Active Ingredients

Active Ingredients Purpose

Aesculus hip: Haemorrhoids, with sharp shooting pains up the back

Andrographis peniculata Frequent urging for stool

Carduus marianus Haemorrhagic piles, prolapse of rectum, burning pain in anus and rectum

Ceanothus americanus Bearing down in abdomen and rectum

Chelidonium majus Burning and itching of anus.

Chionanthus virginiana Constipation

Hamamelis virgiana Haemorrhoids, bleeding profusely, with soreness

INACTIVE INGREDIENT

Water

Warnings

Do not:

use if you have an allergy or hypersensitivity to components of the formula
use if pregnant or nursing

Stop use and ask a doctor if:

condition worsens
If symptoms persists for more than 7 days

Warnungs:

Do not:

- use if you have an allergy or hypersensitivity to components of the formula
- use if pregnant or nursing

Stop use and ask a doctor if:

- condition worsens
- If symptoms persists for more than 7 days

Purpose

Assists in temporarily relief of following symptoms:

Haemorrhoids, with sharp shooting pains up the back

Frequent urging for stool

Haemorrhagic piles, prolapse of rectum, burning pain in anus and rectum

Bearing down in abdomen and rectum

Burning and itching of anus.

Constipation

Haemorrhoids, bleeding profusely, with soreness